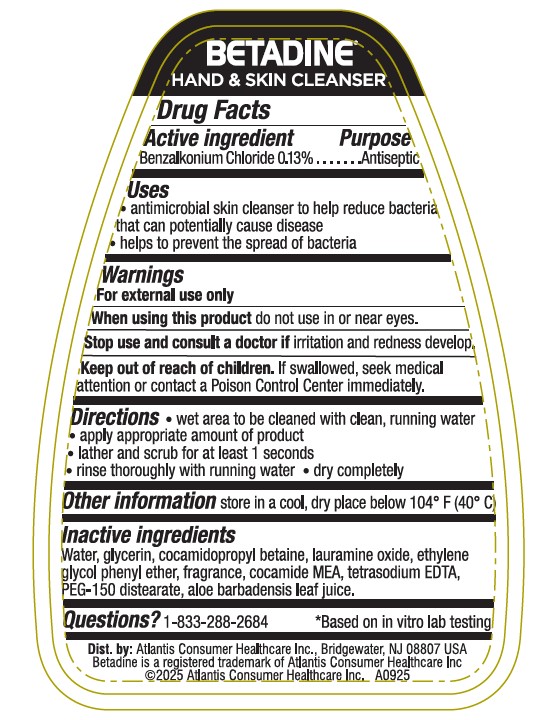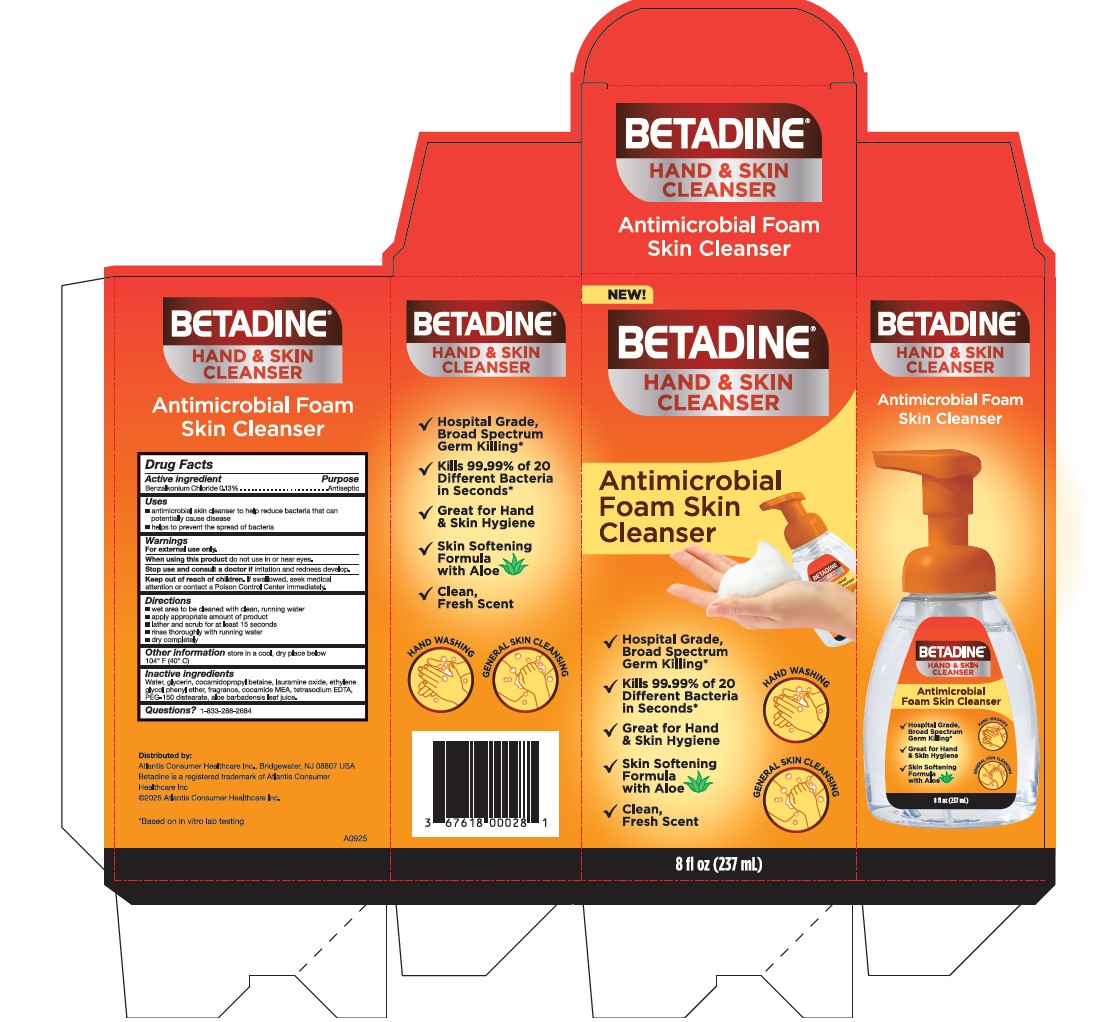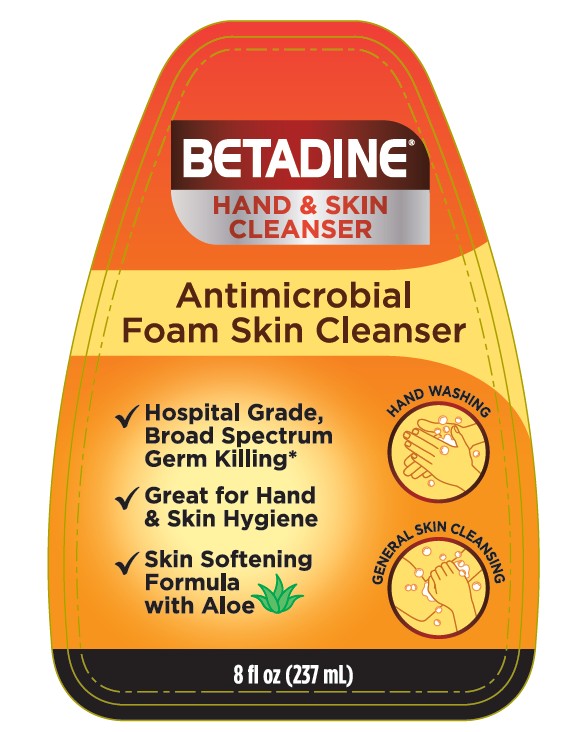 DRUG LABEL: Betadine Foam Cleanser
NDC: 67618-184 | Form: AEROSOL, FOAM
Manufacturer: Atlantis Consumer Healthcare, Inc.
Category: otc | Type: HUMAN OTC DRUG LABEL
Date: 20251205

ACTIVE INGREDIENTS: Benzalkonium Chloride 0.13 g/100 mL
INACTIVE INGREDIENTS: Water; Glycerin; Cocamidopropyl Betaine; Lauramine Oxide; Phenoxyethanol; Coco Monoethanolamide; Edetate Sodium; Peg-150 Distearate; Aloe Vera Leaf Juice

BETADINE®
HAND & SKIN CLEANSER

Drug Facts

Active ingredient

Benzalkonium Chloride 0.13%

Purpose

Antiseptic

Uses

- antimicrobial skin cleanser to help reduce bacteria that can potentially cause disease
- helps to prevent the spread of bacteria

Warnings

For external use only

When using this product

do not use in or near eyes.

Stop use and ask a doctor if

irritation and redness develop.

Keep out of reach of children.

If swallowed, seek medical attention or contact a Poison Control Center immediately.

Directions

- wet area to be cleaned with clean, running water
- apply appropriate amount of product
- lather and scrub for at least 1 seconds
- rinse thoroughly with running water
- dry completely

Other information

Store in a cool, dry place below 104° F (40° C)

Inactive ingredients

Water, glycerin, cocamidopropyl betaine, lauramine oxide, ethylene glycol phenyl ether, fragrance, cocamide MEA, tetrasodium EDTA, PEG-150 distearate, aloe barbadensis leaf juice.

Questions?

1-833-288-2684

Package Labels

BETADINE®
HAND & SKIN
CLEANSER
Antimicrobial
Foam Skin Cleanser
Hospital Grade,
Broad Spectrum
Germ Killing*
Great for Hand
& Skin Hygiene
Skin Softening
Formula
with Aloe
HAND WASHING
GENERAL SKIN CLEANSING
8 fl oz (237 mL)

BETADINE®
HAND & SKIN CLEANSER
*Based on in vitro lab testing
Dist. by: Atlantis Consumer Healthcare Inc., Bridgewater, NJ 08807 USA
Betadine is a registered trademark of Atlantis Consumer Healthcare Inc
© 2025 Atlantis Healthcare Inc. A0925

BETADINE®
HAND & SKIN
CLEANSER
Antimicrobial Foam
Skin Cleanser
NEW!
Hospital Grade,
Broad Spectrum
Germ Killing*
Kills 99.9% of 20
Different Bacteria
in Seconds*
Great for Hand
& Skin Hygiene
Skin Softening
Formula
with Aloe
HAND WASHING
GENERAL SKIN CLEANSING
8 fl oz (237 mL)
Distributed by:
Atlantis Consumer Healthcare Inc., Bridgewater, NJ 08807 USA
Betadine is a registered trademark of Atlantis Consumer
Healthcare Inc.
© 2025 Atlantis Health Care Inc.
*Based on in vitro lab testing
A0925